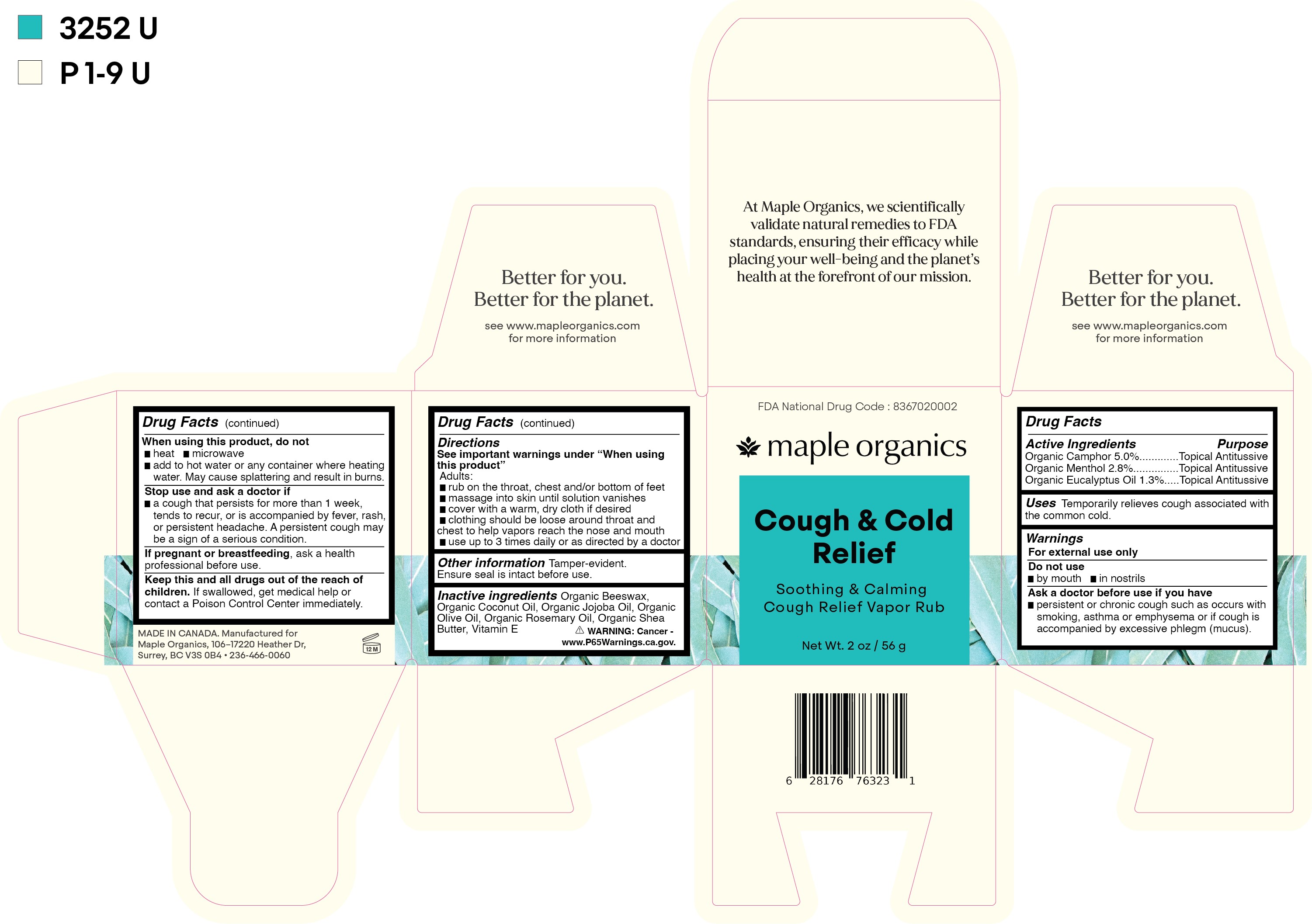 DRUG LABEL: Cough and Cold Therapy
NDC: 83670-200 | Form: OINTMENT
Manufacturer: Everlaan Organics Inc
Category: otc | Type: HUMAN OTC DRUG LABEL
Date: 20250127

ACTIVE INGREDIENTS: MENTHOL 2.8 g/100 g; EUCALYPTUS OIL 1.3 g/100 g; CAMPHOR (NATURAL) 5 g/100 g
INACTIVE INGREDIENTS: ROSEMARY OIL; SHEA BUTTER; COCONUT OIL; YELLOW WAX; OLIVE OIL; JOJOBA OIL; .ALPHA.-TOCOPHEROL

Cough & Cold Relief

Active ingredients

Organic Camphor 5.0%

Organic Menthol 2.8%

Organic Eucalyptus Oil 1.3%

Purpose

Organic Camphor 5.0%.......................Topical Antitussive

Organic Menthol 2.8%.........................Topical Antitussive

Organic Eucalyptus Oil 1.3%...............Topical Antitussive

Uses

Temporarily relieves cough associated with the common cold.

Warnings

For external use only

Do not use

- by mouth
- in nostrils

Ask a doctor before use if you have

- persistent or chronic cough such as occurs with smoking, asthma or emphysema or if cough is accompanied by excessive phlegm (mucus).

When using this product, do not

- heat
- microwave
- add to hot water or any container where heating water. May cause splattering and result in burns.

Stop use and ask a doctor if

- a cough that persists for more than 1 week, tends to recur, or is accompanied by fever, rash, or persistent headache. A persistent cough may be a sign of a serious condition.

PREGNANCY OR BREAST FEEDING

If pregnant or breastfeeding, ask a health professional before use.

KEEP OUT OF REACH OF CHILDREN

Keep this and all drugs out of the reach of children. If swallowed, get medical help or contact a Poison Control Center immediately.

Directions

See important warnings under "When using this product"

Adults:

- rub on the throat, chest and/or bottom of feet
- massage into skin until solution vanishes
- cover with a warm, dry cloth if desired
- clothing should be loose about throat and chest to help vapors reach the nose and mouth
- use up to 3 times daily or as directed by a doctor

Other information

Tamper-evident. Ensure seal is intact before use.

Inactive ingredients

Organic Beeswax, Organic Coconut Oil, Organic Jojoba Oil, Organic Olive Oil, Organic Rosemary Oil, Organic Shea Butter, Vitamin E.

PACKAGE LABEL

maple organics

Cough & Cold Relief

Soothing & Calming Cough Relief Vapor Rub

Net Wt. 2oz / 56 g